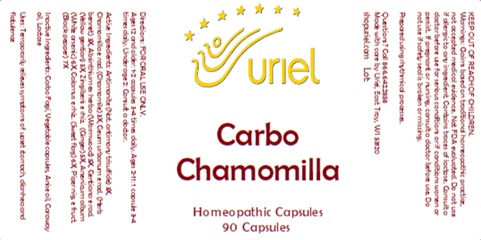 DRUG LABEL: Carbo Chamomilla
NDC: 48951-3216 | Form: CAPSULE
Manufacturer: Uriel Pharmacy Inc.
Category: homeopathic | Type: HUMAN OTC DRUG LABEL
Date: 20241115

ACTIVE INGREDIENTS: ANTIMONY TRISULFIDE 3 [hp_X]/1 1; MATRICARIA RECUTITA 3 [hp_X]/1 1; WORMWOOD 5 [hp_X]/1 1; GENTIANA LUTEA ROOT 5 [hp_X]/1 1; ARSENIC TRIOXIDE 6 [hp_X]/1 1; ACORUS CALAMUS ROOT 6 [hp_X]/1 1; GEUM URBANUM ROOT 3 [hp_X]/1 1; GINGER 5 [hp_X]/1 1; BLACK PEPPER 7 [hp_X]/1 1
INACTIVE INGREDIENTS: ACTIVATED CHARCOAL; POWDERED CELLULOSE; ANISE OIL; CARAWAY OIL; LACTOSE, UNSPECIFIED FORM

Carbo Chamomilla

INDICATIONS AND USAGE

Directions: FOR ORAL USE ONLY.

DOSAGE AND ADMINISTRATION

Ages 12 and older: 1-2 capsules 3-4 times daily. Ages 2-11: 1 capsule 3-4 times daily. Under age 2: Consult a doctor.

ACTIVE INGREDIENT

Active Ingredients: Antimonite (Nat. antimony trisulfide) 3X, Chamomilla e rad. (Chamomile) 3X, Geum urbanum e rad. (Herb bennet) 3X, Absinthium ex herba (Wormwood) 5X, Gentiana e rad. (Yellow gentian) 5X, Zingiberis e rhiz. (Ginger) 5X, Arsenicum album (White arsenic) 6X, Calamus e rhiz. (Sweet flag) 6X, Piper nig. e fruct. (Black pepper) 7X

INACTIVE INGREDIENT

Inactive Ingredients: Carbo Fagi, Vegetable capsules, Anise oil, Caraway oil, Lactose

Prepared using rhythmical processes.

PURPOSE

Uses: Temporarily relieves symptoms of upset stomach, diarrhea and flatulence

KEEP OUT OF REACH OF CHILDREN.

WARNINGS

Warnings: Claims based on traditional homeopathic practice, not accepted medical evidence. Not FDA evaluated. Do not use if allergic to any ingredient. Contains traces of lactose. Consult a doctor before use for serious conditions or if conditions worsen or persist. If pregnant or nursing, consult a doctor before use. Do not use if safety seal is broken or missing.

Questions? Call 866.642.2858
Made with care by Uriel, East Troy, WI 53120
shopuriel.com Lot: